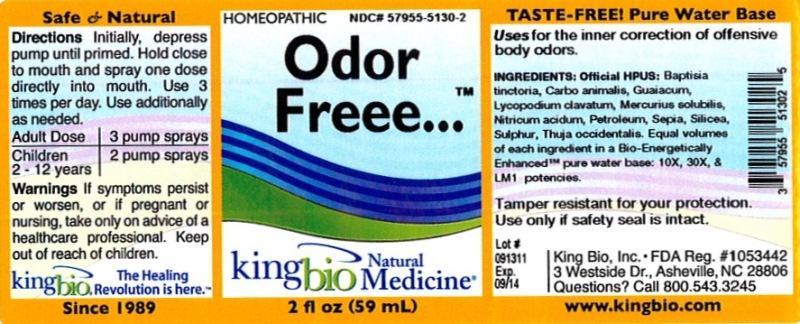 DRUG LABEL: Odor Freee
NDC: 57955-5130 | Form: LIQUID
Manufacturer: King Bio Inc.
Category: homeopathic | Type: HUMAN OTC DRUG LABEL
Date: 20121003

ACTIVE INGREDIENTS: BAPTISIA TINCTORIA ROOT 10 [hp_X]/59 mL; CARBO ANIMALIS 10 [hp_X]/59 mL; GUAIACUM OFFICINALE RESIN 10 [hp_X]/59 mL; LYCOPODIUM CLAVATUM SPORE 10 [hp_X]/59 mL; MERCURIUS SOLUBILIS 10 [hp_X]/59 mL; NITRIC ACID 10 [hp_X]/59 mL; KEROSENE 10 [hp_X]/59 mL; SEPIA OFFICINALIS JUICE 10 [hp_X]/59 mL; SILICON DIOXIDE 10 [hp_X]/59 mL; SULFUR 10 [hp_X]/59 mL; THUJA OCCIDENTALIS LEAFY TWIG 10 [hp_X]/59 mL
INACTIVE INGREDIENTS: WATER

Odor Freee

Active Ingredients

Official HPUS: Baptisia tinctoria, Carbo animalis, Guaiacum, Lycopodium clavatum, Mercurius solubilis, Nitricum acidum, Petroleum, Sepia, Silicea, Sulphur and Thuja occidentalis.

Inactive Ingredient

Equal volumes of each ingredient in a Bio-Energetically Enhanced pure water base: 10X, 30X and LM1 potencies.

Purpose

Uses for the inner correction of offensive body odors.

Dosage and Administration

Directions: Initially, depress pump until primed. Hold close to mouth and spray one dose directly into mouth. Use 3 times per day. Use additionally as needed.

Adult Dose 3 pump sprays

Children 2 - 12 years 2 pump sprays

Warnings

If symptoms persist or worsen, or if pregnant or nursing, take only on advice of a healthcare professional. Keep out of reach of children.

Other: Tamper resistant for your protection. Use only if safety seal is intact.

Keep out of reach of children.

Indications and Usage

Uses for the inner correction of offensive body odors.

PACKAGE LABEL

King Bio Inc.

3 Westside Drive

Asheville, NC 28806

Questions? Call 800.543.3245

www.kingbio.com